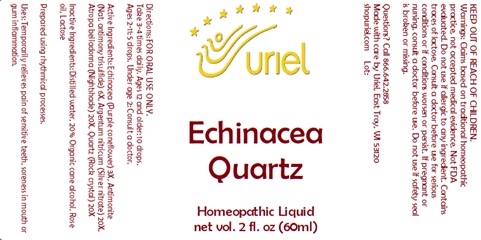 DRUG LABEL: Echinacea Quartz
NDC: 48951-4020 | Form: LIQUID
Manufacturer: Uriel Pharmacy, Inc.
Category: homeopathic | Type: HUMAN OTC DRUG LABEL
Date: 20241122

ACTIVE INGREDIENTS: ANTIMONY TRISULFIDE 6 [hp_X]/1 mL; SILVER 20 [hp_X]/1 mL; SILICON DIOXIDE 20 [hp_X]/1 mL; ECHINACEA, UNSPECIFIED 3 [hp_X]/1 mL; ATROPA BELLADONNA 20 [hp_X]/1 mL
INACTIVE INGREDIENTS: WATER; ROSE OIL; LACTOSE, UNSPECIFIED FORM; ALCOHOL

Echinacea Quartz

INDICATIONS AND USAGE

Directions: FOR ORAL USE ONLY.

DOSAGE AND ADMINISTRATION

Take 3-4 times daily. Ages 12 and older: 10 drops. Ages 2-11: 5 drops. Under age 2: Consult a doctor.

ACTIVE INGREDIENT

Active Ingredients: Echinacea (Purple coneflower) 3X, Antimonite (Nat. antimony trisulfide) 6X, Argentum nitricum (Silver nitrate) 20X, Atropa belladonna (Nightshade) 20X, Quartz (Rock crystal) 20X

INACTIVE INGREDIENT

Inactive Ingredients: Distilled water, 20% Organic cane alcohol, Rose oil, Lactose

Prepared using rhythmical processes

PURPOSE

Uses: Temporarily relieves pain of sensitive teeth, soreness in mouth or gum inflammation.

KEEP OUT OF REACH OF CHILDREN.

WARNINGS

Warnings: Claims based on traditional homeopathic practice, not accepted medical evidence. Not FDA evaluated. Do not use if allergic to any ingredient. Contains traces of lactose. Consult a doctor before use for serious conditions or if conditions worsen or persist. If pregnant or nursing, consult a doctor before use. Do not use if safety seal is broken or missing.

Questions? Call 866.642.2858
Made with care by Uriel, East Troy, WI 53120
shopuriel.com Lot: